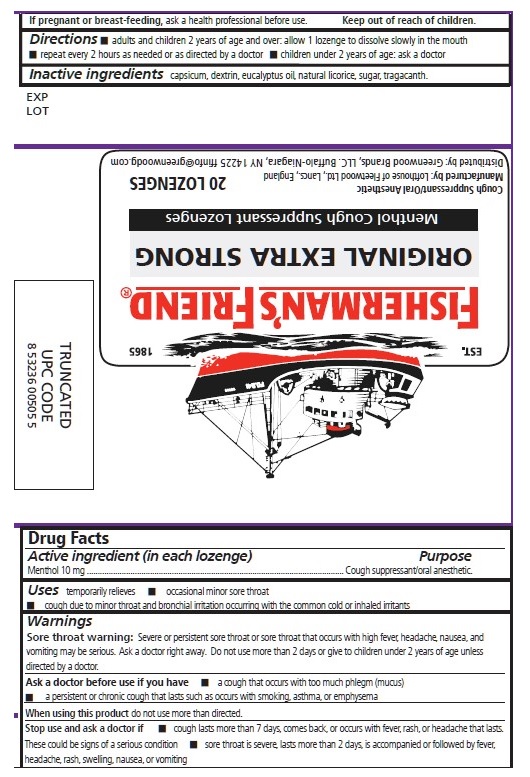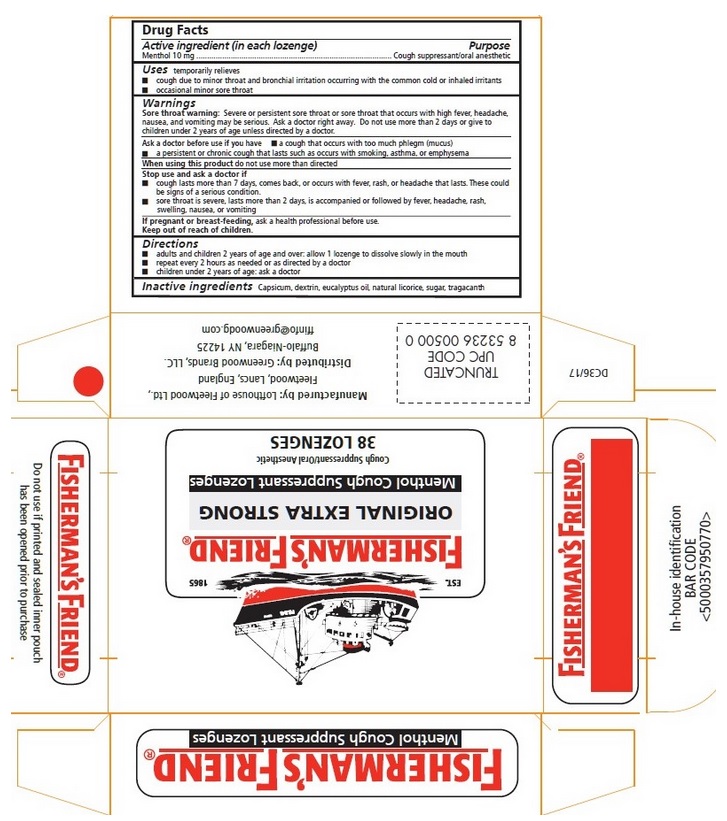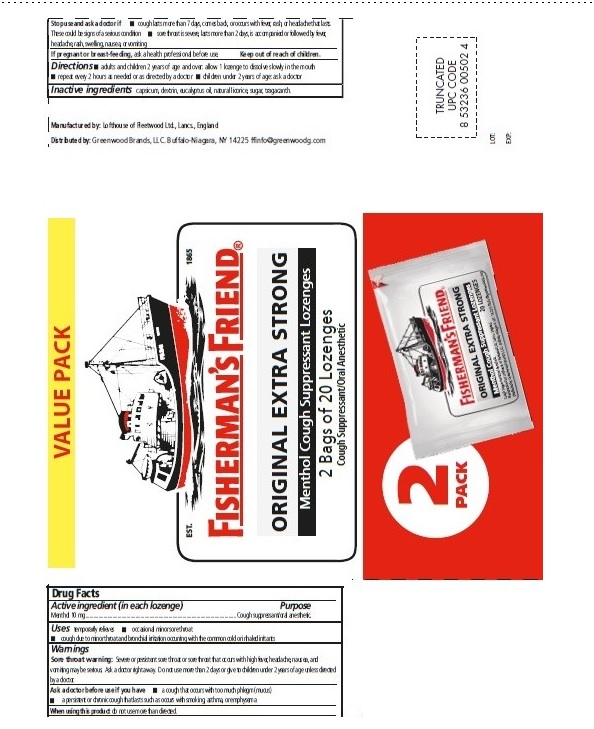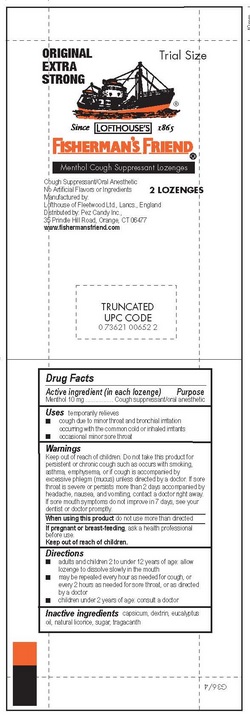 DRUG LABEL: Original Extra Strong All Natural Fishermans Friend Menthol Cough Suppressant
NDC: 55711-064 | Form: LOZENGE
Manufacturer: Lofthouse of Fleetwood, Ltd.
Category: otc | Type: HUMAN OTC DRUG LABEL
Date: 20250930

ACTIVE INGREDIENTS: MENTHOL 10 mg/1 1
INACTIVE INGREDIENTS: CAPSICUM; EUCALYPTUS OIL; LICORICE; RAW SUGAR; TRAGACANTH

Original Extra Strong Lozenges

Active ingredient (in each lozenge)

Menthol 10 mg

Purpose

Cough suppressant/oral anesthetic

Uses

temporarily relieves

- occasional minor sore throat
- cough due to minor throat and bronchial irritation occurring with the common cold or inhaled irritants

Warnings

Sore throat warning: Severe or persistent sore throat or sore throat that occurs with high fever, headache, nausea, and vomiting may be serious. Ask a doctor right away. Do not use more than 2 days or give to children under 2 years of age unless directed by a doctor.

Ask a doctor before use if you have

- a cough that occurs with too much phlegm (mucus)
- a persistent or chronic cough that lasts such as occurs with smoking, asthma, or emphysema

When using this product
do not use more than directed

Stop use and ask a doctor if

- cough lasts more than 7 days, comes back, or occurs with fever, rash, or headache that lasts. These could be signs of a serious condition.
- sore throat is severe, lasts more than 2 days, is accompanied or followed by fever, headache, rash, swelling, nausea, or vomiting

PREGNANCY OR BREAST FEEDING

If pregnant or breast-feeding, ask a health professional before use

Keep out of reach of children.

Directions

- adults and children 2 years of age and over: allow 1 lozenge to dissolve slowly in the mouth
- repeat every 2 hours as needed or as directed by a doctor
- children under 2 years of age: ask a doctor

Inactive ingredients

capsicum, dextrin, eucalyptus oil, natural licorice, sugar, tragacanth

FISHERMAN'S FRIEND®

ORIGINAL EXTRA STRONG

Menthol Cough Suppressant Lozenges

Cough Suppresant/Oral Anesthetic

Manufactured by: Lofthouse of Fleetwood Ltd., Lancs, England

Distributed by: Greenwood Brands, LLC. Buffalo-Niagara, NY 14225

ffinfo@greenwoodg.com